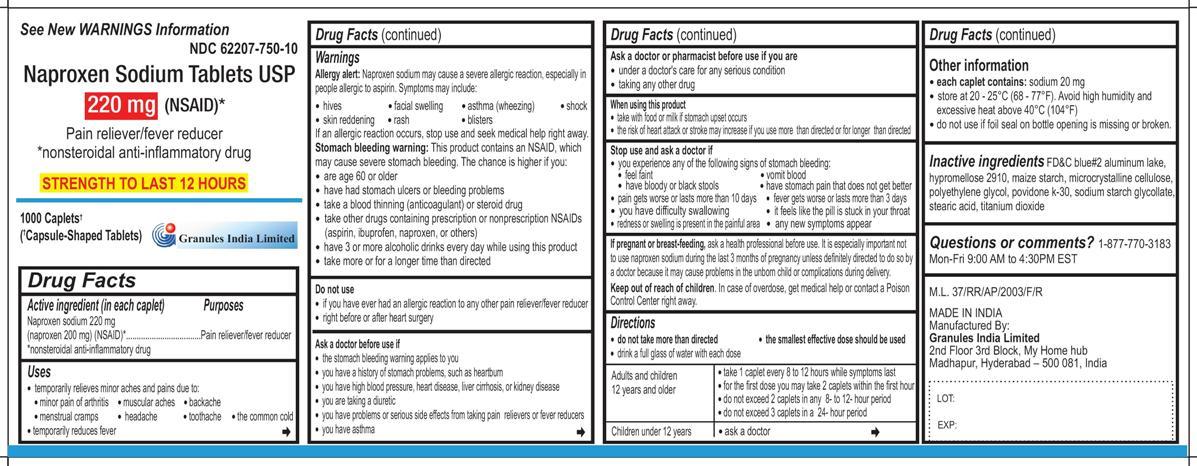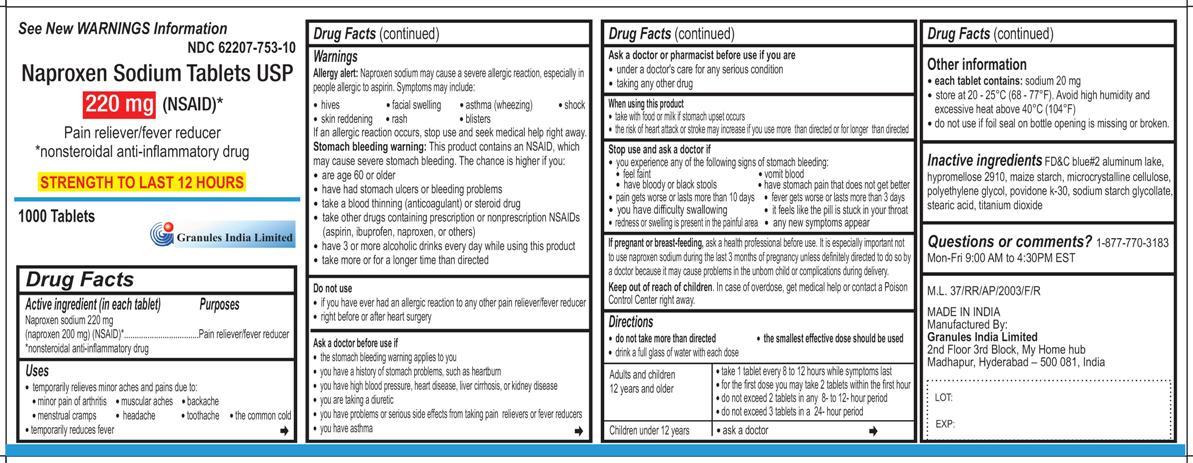 DRUG LABEL: Naproxen Sodium
NDC: 62207-750 | Form: TABLET
Manufacturer: Granules India Limited
Category: otc | Type: HUMAN OTC DRUG LABEL
Date: 20231211

ACTIVE INGREDIENTS: NAPROXEN SODIUM 220 mg/1 1
INACTIVE INGREDIENTS: CELLULOSE, MICROCRYSTALLINE; STARCH, CORN; POVIDONE K30; SODIUM STARCH GLYCOLATE TYPE A POTATO; STEARIC ACID; HYPROMELLOSES; POLYETHYLENE GLYCOL 400; TITANIUM DIOXIDE; FD&C BLUE NO. 2

Naproxen Sodium Tablets

ACTIVE INGREDIENT

Naproxen sodium 220 mg

(naproxen 200 mg) (NSAID)*

*nonsteroidal anti-inflammatory drug

PURPOSE

Pain reliever/fever reducer

INDICATIONS AND USAGE

- temporarily relieves minor aches and pains due to:
- minor pain of arthritis
- muscular aches
- backache
- menstrual cramps
- headache
- toothache
- the common cold
- temporarily reduces fever

WARNINGS

Allergy alert: Naproxen sodium may cause a severe allergic reaction, especially in people allergic to aspirin. Symptoms may include:

- hives
- facial swelling
- asthma (wheezing)
- shock
- skin reddening
- rash
- blisters

If an allergic reaction occurs, stop use and seek medical help right away.

Stomach bleeding warning: This product contains an NSAID, which may cause severe stomach bleeding. The chance is higher if you:

- are age 60 or older
- have had stomach ulcers or bleeding problems
- take a blood thinning (anticoagulant) or steroid drug
- take other drugs containing prescription or nonprescription NSAIDs (aspirin, ibuprofen, naproxen, or others)
- have 3 or more alcoholic drinks every day while using this product
- take more or for a longer time than directed

DO NOT USE

- if you have ever had an allergic reaction to any other pain reliever/fever reducer
- right before or after heart surgery

ASK DOCTOR

- the stomach bleeding warning applies to you
- you have a history of stomach problems, such as heartburn
- you have high blood pressure, heart disease, liver cirrhosis, or kidney disease
- you are taking a diuretic
- you have problems or serious side effects from taking pain relievers or fever reducers
- you have asthma

ASK DOCTOR/PHARMACIST

- under a doctor’s care for any serious condition
- taking any other drug

WHEN USING

- take with food or milk if stomach upset occurs
- the risk of heart attack or stroke may increase if you use more than directed or for longer than directed

STOP USE

- you experience any of the following signs of stomach bleeding:
- feel faint
- vomit blood
- have bloody or black stools
- have stomach pain that does not get better
- pain gets worse or lasts more than 10 days
- fever gets worse or lasts more than 3 days
- you have difficulty swallowing
- it feels like the pill is stuck in your throat
- you develop heartburn
- redness or swelling is present in the painful area
- any new symptoms appear

PREGNANCY OR BREAST FEEDING

Ask a health professional before use. It is especially important not to use naproxen sodium during the last 3 months of pregnancy unless definitely directed to do so by a doctor because it may cause problems in the unborn child or complications during delivery.

KEEP OUT OF REACH OF CHILDREN

In case of overdose, get medical help or contact a Poison Control Center right away.

DOSAGE AND ADMINISTRATION

- do not take more than directed
- the smallest effective dose should be used
- drink a full glass of water with each dose

Adults and children 12 years and older | take 1 caplet every 8 to 12 hours while symptoms last for the first dose you may take 2 caplets within the first hour do not exceed 2 caplets in any 8- to 12-hour period do not exceed 3 caplets in a 24-hour period
Children under 12 years | ask a doctor

Information for Patients

- each tablet contains: sodium 20 mg
- store at 20 - 25°C (68 - 77°F). Avoid high humidity and excessive heat above 40°C (104°F)
- do not use if foil seal on bottle opening is missing or broken.

INACTIVE INGREDIENT

FD&C blue#2 aluminum lake, hypromellose 2910, maize starch, microcrystalline cellulose, polyethylene glycol, povidone k-30, sodium starch glycolate, stearic acid, titanium dioxide

QUESTIONS

1-877-770-3183 Mon – Fri 9:00 AM to 4:00 PM EST

M.L. 37/RR/AP/2003/F/R

MADE IN INDIA

Manufactured By:

Granules India Limited

2nd Floor 3rd Block, My Home hub

Madhapur, Hyderabad – 500 081, India